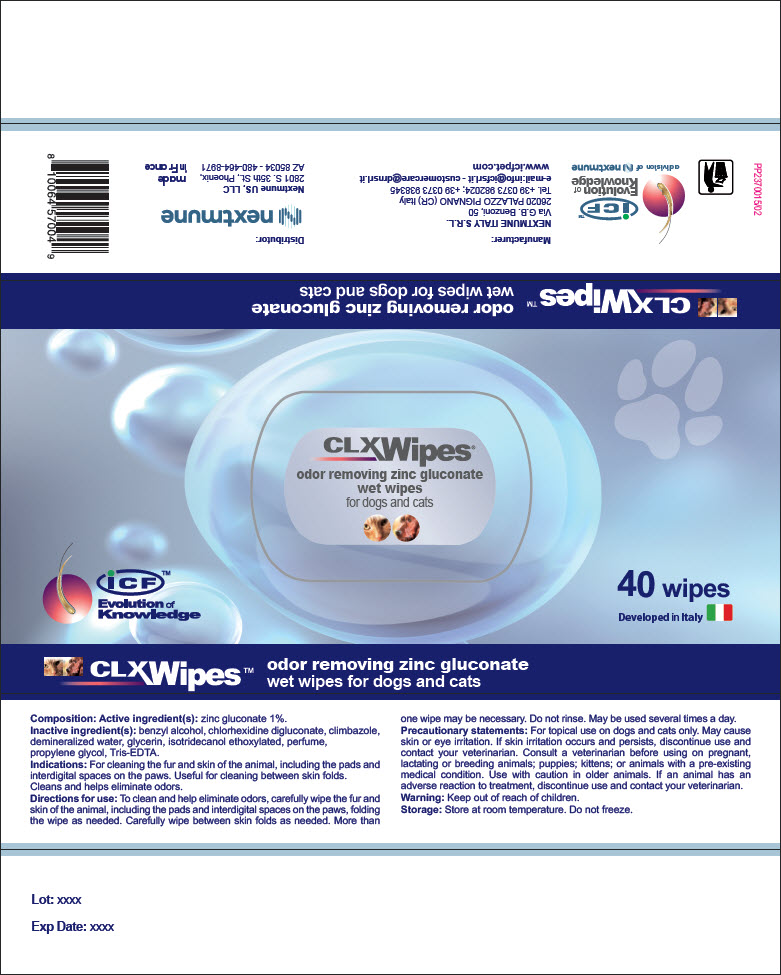 DRUG LABEL: CLX Wipes
NDC: 86127-005 | Form: CLOTH
Manufacturer: Nextmune AB
Category: animal | Type: OTC ANIMAL DRUG LABEL
Date: 20220517

ACTIVE INGREDIENTS: ZINC GLUCONATE 10 mg/1 mL
INACTIVE INGREDIENTS: water; CHLORHEXIDINE GLUCONATE; propylene glycol; glycerin; TROMETHAMINE; EDETATE SODIUM; ISOTRIDECYL ALCOHOL; BENZYL ALCOHOL; CLIMBAZOLE

CLX Wipes®

VETERINARY INDICATIONS

odor removing zinc gluconate
wet wipes for dogs and cats

Composition: Active ingredient(s): zinc gluconate 1%.

Inactive ingredient(s): benzyl alcohol, chlorhexidine digluconate, climbazole, demineralized water, glycerin, isotridecanol ethoxylated, perfume, propylene glycol, Tris-EDTA.

INDICATIONS AND USAGE

Indications: For cleaning the fur and skin of the animal, including the pads and interdigital spaces on the paws. Useful for cleaning between skin folds. Cleans and helps eliminate odors.

DOSAGE AND ADMINISTRATION

Directions for use: To clean and help eliminate odors, carefully wipe the fur and skin of the animal, including the pads and interdigital spaces on the paws, folding the wipe as needed. Carefully wipe between skin folds as needed. More than one wipe may be necessary. Do not rinse. May be used several times a day.

PRECAUTIONS

Precautionary statements: For topical use on dogs and cats only. May cause skin or eye irritation. If skin irritation occurs and persists, discontinue use and contact your veterinarian. Consult a veterinarian before using on pregnant, lactating or breeding animals; puppies; kittens; or animals with a pre-existing medical condition. Use with caution in older animals. If an animal has an adverse reaction to treatment, discontinue use and contact your veterinarian.

Warning: Keep out of reach of children.

Storage: Store at room temperature. Do not freeze.

iCF™
Evolution of
Knowledge
a division of nextmune

Manufacturer:

NEXTMUNE ITALY S.R.L.
Via G.B. Benzoni, 50
26020 PALAZZO PIGNANO (CR) Italy
Tel. +39 0373 982024; +39 0373 938345
e-mail:info@icfsrl.it - customercare@drnsrl.it
www.icfpet.com

Distributor:

Nextmune US, LLC
2801 S. 35th St., Phoenix,
AZ 85034 - 480-464-8971

made
in France

PP2370015/02

PRINCIPAL DISPLAY PANEL - 40 Wipe Container

CLX Wipes®
odor removing zinc gluconate
wet wipes
for dogs and cats

iCF™
Evolution of
Knowledge

40 wipes

Developed in Italy